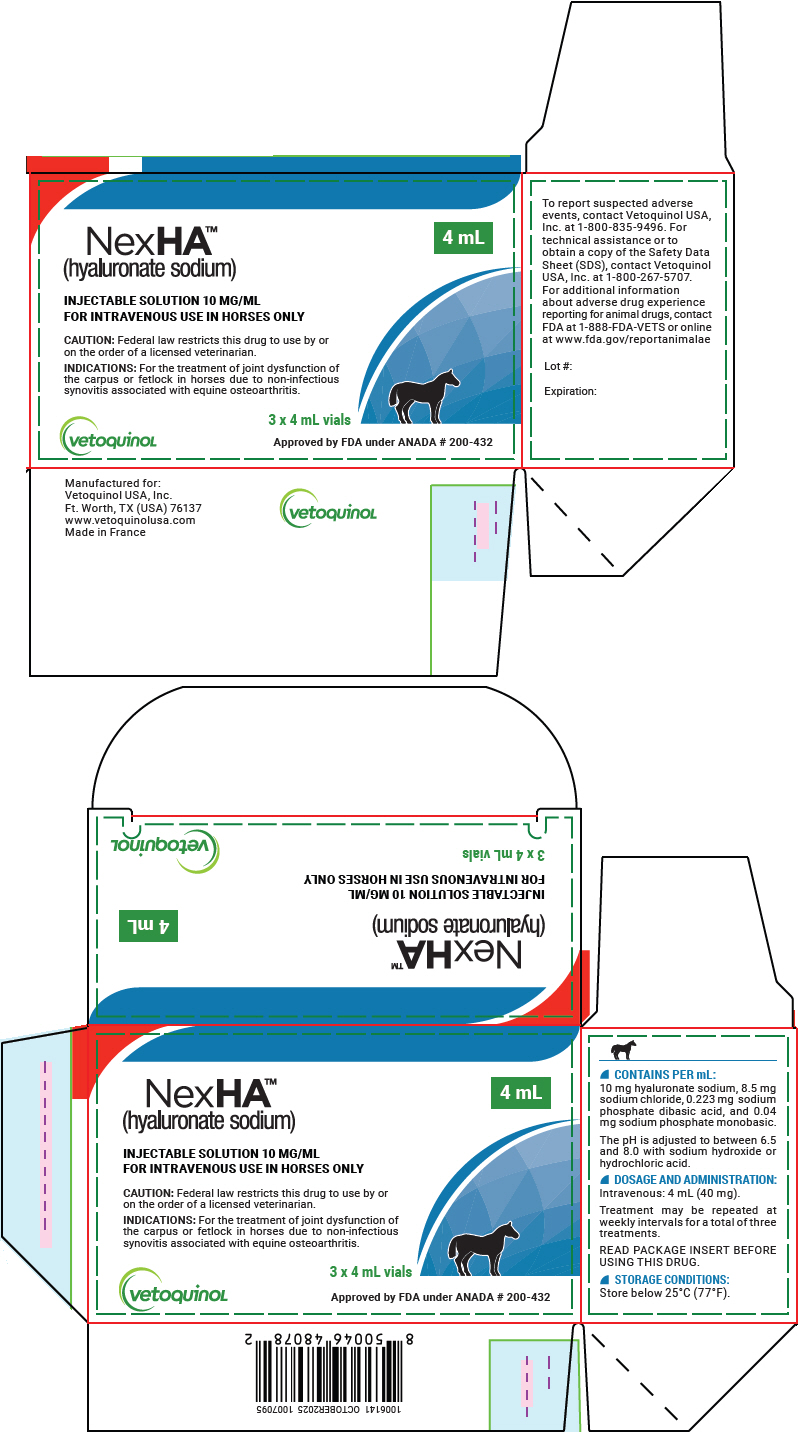 DRUG LABEL: NexHA
NDC: 17030-098 | Form: SOLUTION
Manufacturer: Vetoquinol USA, Inc.
Category: animal | Type: PRESCRIPTION ANIMAL DRUG LABEL
Date: 20251222

ACTIVE INGREDIENTS: HYALURONATE SODIUM 10 mg/1 mL
INACTIVE INGREDIENTS: SODIUM CHLORIDE; SODIUM PHOSPHATE, DIBASIC, DODECAHYDRATE; SODIUM PHOSPHATE, MONOBASIC, DIHYDRATE

NexHA™
(hyaluronate sodium)

Injectable Solution 10 mg/mL
For Intravenous Use in Horses Only

4 mL

PRECAUTIONS

CAUTION: Federal law restricts this drug to use by or on the order of a licensed veterinarian.

DESCRIPTION

DESCRIPTION: NexHA™ injectable solution is a clear, colorless solution of low viscosity.

NexHA™ injectable solution is pyrogen free, sterile and does not contain a preservative. It is administered by intravenous injection. Hyaluronic acid, the conjugate acid of hyaluronate sodium, is extracted from the capsule of Streptococcus spp. and purified, resulting in a form which is essentially free of protein and nucleic acids. NexHA™ injectable solution is supplied in 4 mL (40 mg) vials. Each mL contains 10 mg hyaluronate sodium, 8.5 mg sodium chloride, 0.223 mg sodium phosphate dibasic acid and 0.04 mg sodium phosphate monobasic. The pH is adjusted to between 6.5 and 8.0 with sodium hydroxide or hydrochloric acid.

MECHANISM OF ACTION

CHEMISTRY: Hyaluronic acid, a glycosaminoglycan, can exist in the following forms depending upon the chemical environment in which it is found: as the acid, hyaluronic acid; as the sodium salt, sodium hyaluronate (hyaluronate sodium); or as the hyaluronate anion. These terms may be used interchangeably but in all cases, reference is made to the glycosaminoglycan composed of repeating subunits of D-glucuronic acid and N-acetyl-D-glucosamine linked together by glycosidic bonds. Since this product originates from a microbial source, there is no potential for contamination with dermatan or chondroitin sulfate or any other glycosaminoglycan.

CLINICAL PHARMACOLOGY

CLINICAL PHARMACOLOGY: Hyaluronic acid is a naturally occurring substance present in connective tissue, skin, vitreous humor and the umbilical cord in all mammals. High concentrations of hyaluronic acid are also found in the synovial fluid. It also constitutes the major component of the capsule of certain microorganisms. The hyaluronic acid produced by bacteria is the same structure and configuration as that found in mammals.

The actual mechanism of action for hyaluronate sodium in the healing of degenerative joint disease is not completely understood. One major function appears to be the regulation of normal cellular constituents. This effect decreases the impact of exudation, enzyme release and subsequent degradation of joint integrity. Additionally, hyaluronate sodium exerts an anti-inflammatory action by inhibiting the movement of granulocytes and macrophages.^1

Hyaluronate molecules are long chains which form a filter network interspersed with normal cellular fluids. It is widely accepted that injection directly into the joint pouch enhances the healing of inflamed synovium by restoring lubrication of the joint fluid. This further supplements the visco-elastic properties of normal joint fluid.

VETERINARY INDICATIONS

INDICATIONS: NexHA™ injectable solution is indicated in the treatment of joint dysfunction of the carpus or fetlock in horses due to non-infectious synovitis associated with equine osteoarthritis.

DOSAGE AND ADMINISTRATION: 4 mL (40 mg) injected intravenously. Treatment may be repeated at weekly intervals for a total of three treatments. Use aseptic technique and inject slowly into the jugular vein. Horses should be given stall rest after treatment before gradually resuming normal activity.

Discard any unused portion of the drug and the empty vial after opening.

CONTRAINDICATIONS

CONTRAINDICATIONS: There are no known contraindications for the use of NexHA™ injectable solution in horses.

WARNINGS

WARNING: Do not use in horses intended for human consumption.

WARNINGS

HUMAN WARNINGS: Not for use in humans. Keep this and all other drugs out of reach of children.

WARNINGS

ANIMAL SAFETY WARNING: Not for intra-articular use.

PRECAUTIONS

PRECAUTIONS: Radiographic evaluation should be carried out in cases of acute lameness to ensure that the joint is free from serious fracture.

The safety of NexHA™ injectable solution has not been evaluated in breeding stallions or in breeding, pregnant or lactating mares.

ADVERSE REACTIONS

ADVERSE REACTIONS: No local or systemic side effects were observed in the clinical field studies using hyaluronate sodium injectable solution.

POST-APPROVAL EXPERIENCE: While all adverse reactions are not reported, the following adverse reactions are based on voluntary post-approval reporting for hyaluronate sodium injectable solution: Occasional depression, lethargy, and fever.

To report suspected adverse events, contact Vetoquinol USA, Inc. at 1-800-835-9496. For technical assistance or to obtain a copy of the Safety Data Sheet (SDS), contact Vetoquinol USA, Inc. at 1-800- 267-5707. For additional information about adverse drug experience reporting for animal drugs, contact FDA at 1-888-FDA-VETS or online at www.fda.gov/ reportanimalae.

EFFECTIVENESS: Forty-six horses with lameness in either the carpal or fetlock joints were treated intravenously or intra-articularly with hyaluronate sodium injectable solution in a well controlled clinical field trial conducted at four locations. One, two or three injections were given based on clinical improvement. Overall clinical improvement was judged as excellent or good in 90% of the cases treated intravenously and 96% of those treated intra-articularly with hyaluronate sodium injectable solution.

ANIMAL PHARMACOLOGY AND OR TOXICOLOGY

ANIMAL SAFETY: Hyaluronate sodium injectable solution was administered to normal horses at one, three and five times the recommended intra-articular dosage of 20 mg and the intravenous dosage of 40 mg. Treatments were given once weekly for nine consecutive weeks (three times the maximum duration). No systemic clinical signs were observed nor were there any adverse effects upon hematology or clinical chemistry parameters. A transient, slight to mild post-injection swelling of the joint capsule occurred in some of the animals treated intra-articularly with hyaluronate sodium injectable solution as it did in the saline treated control horses. No gross or histological lesions were observed in the soft tissues or the surface areas of the treated joint.

STORAGE: Store below 25°C (77°F).

HOW SUPPLIED

HOW SUPPLIED: NexHA™ injectable solution is supplied in cartons containing three x 4 mL (40 mg) vials and twelve x 4 mL (40 mg) vials

Manufactured for:
Vetoquinol USA, Inc.
4250 N. Sylvania Ave.
Ft. Worth, TX (USA) 76137
www.vetoquinolusa.com

REFERENCES

REFERENCES: ^1Swanstrom, O.G. 1978. Hyaluronate (hyaluronic acid) and its use, Proc. American Assoc. Equine Pract., 24th annual convention, pp. 345-348.

Approved by FDA under ANADA # 200-432
Made in France
439313/1006141 November2025
1007097

vetoquinoL
ACHIEVE MORE TOGETHER

PRINCIPAL DISPLAY PANE - 4 mL Vial Carton

4 mL

NexHA™
(hyaluronate sodium)

INJECTABLE SOLUTION 10 MG/ML
FOR INTRAVENOUS USE IN HORSES ONLY

CAUTION: Federal law restricts this drug to use by or
on the order of a licensed veterinarian.

INDICATIONS: For the treatment of joint dysfunction of
the carpus or fetlock in horses due to non-infectious
synovitis associated with equine osteoarthritis.

3 x 4 mL vials

vetoquinoL

Approved by FDA under ANADA # 200-432